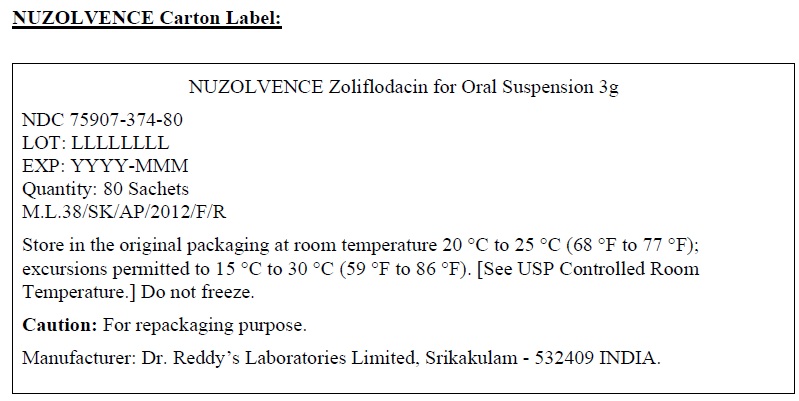 DRUG LABEL: Nuzolvence
NDC: 75907-374 | Form: GRANULE
Manufacturer: Dr. Reddy's Laboratories Inc.
Category: other | Type: BULK INGREDIENT
Date: 20260129

ACTIVE INGREDIENTS: ZOLIFLODACIN 3 g/3 g
INACTIVE INGREDIENTS: MICROCRYSTALLINE CELLULOSE; MANNITOL; CROSCARMELLOSE SODIUM; SILICON DIOXIDE; XANTHAN GUM; TALC; MAGNESIUM STEARATE

BULK INGREDIENT TEMPLATE

PRINCIPAL DISPLAY PANEL

NUZOLVENCE Zoliflodacin for Oral Suspension 3g